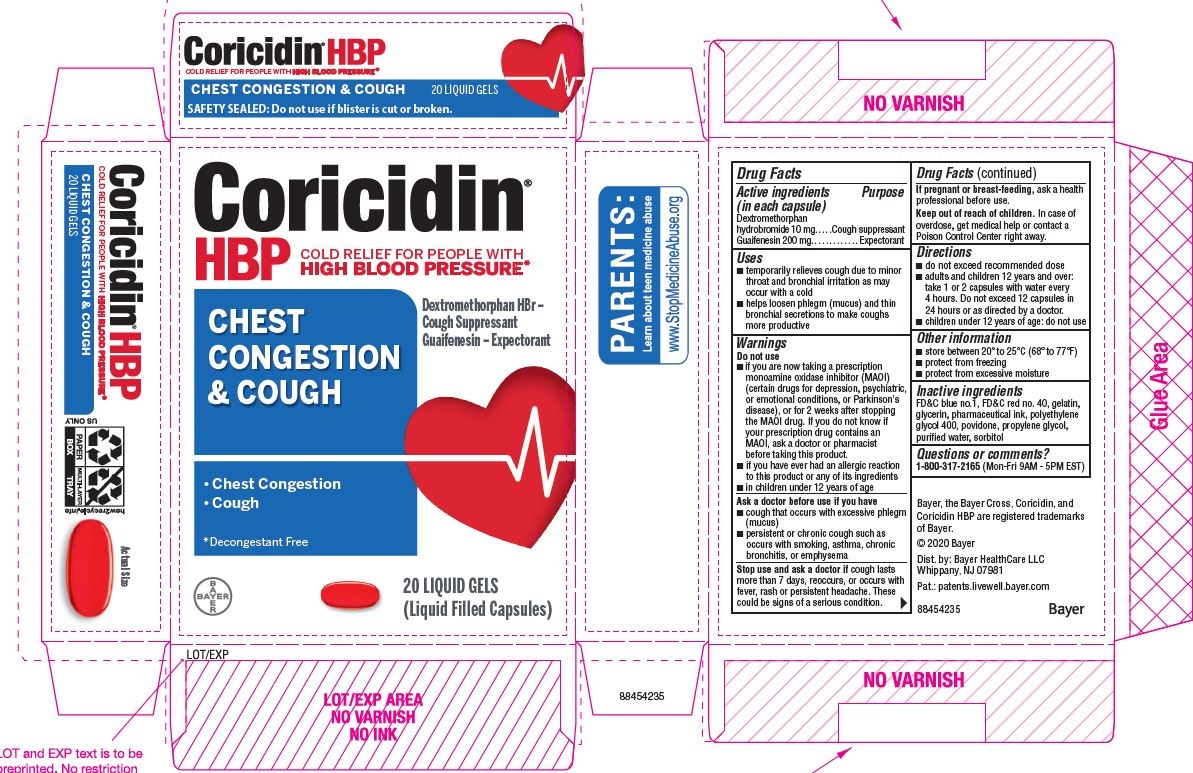 DRUG LABEL: Coricidin HBP Chest Congestion And Cough
NDC: 11523-7158 | Form: CAPSULE, GELATIN COATED
Manufacturer: Bayer HealthCare LLC.
Category: otc | Type: HUMAN OTC DRUG LABEL
Date: 20251205

ACTIVE INGREDIENTS: DEXTROMETHORPHAN HYDROBROMIDE 10 mg/1 1; GUAIFENESIN 200 mg/1 1
INACTIVE INGREDIENTS: SODIUM HYDROXIDE; SHELLAC; POLYETHYLENE GLYCOL, UNSPECIFIED; SORBITAN; TITANIUM DIOXIDE; FD&C RED NO. 40; GELATIN; GLYCERIN; POVIDONE; PROPYLENE GLYCOL; SORBITOL; WATER

Coricidin® HBP Chest Congestion & Cough

Drug Facts

Active ingredients (in each capsule) | Purpose
Dextromethorphan hydrobromide 10 mg | Cough suppressant
Guaifenesin 200 mg | Expectorant

Uses

- temporarily relieves cough due to minor throat and bronchial irritation as may occur with a cold
- helps loosen phlegm (mucus) and thin bronchial secretions to make coughs more productive

Warnings

Do not use

- if you are now taking a prescription monoamine oxidase inhibitor (MAOI) (certain drugs for depression, psychiatric, or emotional conditions, or Parkinson's disease), or for 2 weeks after stopping the MAOI drug. If you do not know if your prescription drug contains an MAOI, ask a doctor or pharmacist before taking this product.
- if you have ever had an allergic reaction to this product or any of its ingredients

Ask a doctor before use if you have

- cough that occurs with excessive phlegm (mucus)
- persistent or chronic cough as occurs with smoking, asthma, chronic bronchitis, or emphysema

Stop use and ask a doctor if cough lasts more than 7 days, reoccurs, or occurs with fever, rash or persistent headache. These could be signs of a serious condition.

PREGNANCY OR BREAST FEEDING

If pregnant or breast-feeding, ask a health professional before use.

Keep out of reach of children. In case of overdose, get medical help or contact a Poison Control Center right away. Abuse of this product can lead to serious injury.

Directions

- do not exceed recommended dose
- adults and children 12 years and over:
  1 or 2 capsules every 4 hours, not more than
  12 capsules in 24 hours
- children under 12 years of age: ask a doctor

Other information

- store between 20° to 25°C (68° to 77°F)
- protect from freezing
- protect from excessive moisture

Inactive ingredients

FD&C red no. 40, gelatin, glycerin, polyethylene glycol, povidone, propylene glycol, purified water, shellac, sodium, sorbitol sorbitan solution, titanium dioxide.

Questions or comments?

Call 1-800-317-2165 between 8:00 AM and 5:00 PM Central Standard Time, Monday through Friday

PRINCIPAL DISPLAY PANEL - 2 x 10 Softgel Blister Pack Carton

Coricidin®
HBP

COLD SYMPTOM RELIEF for people with
HIGH BLOOD PRESSURE

CHEST
CONGESTION
& COUGH

Relieves:

- Chest Congestion
- Cough

Guaifenesin - Expectorant,

Dextromethorphan hydrobromide -

cough suppressent

CONTROLS COUGH
FAST

Liqui-Gels®

DECONGESTANT-FREE

American Heart Association

Health Information Enclosed

20 LIQUID GELS

(Liquid Filled Capsules)